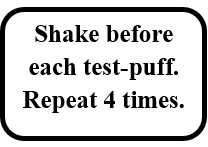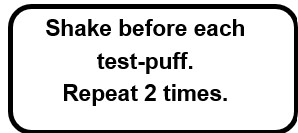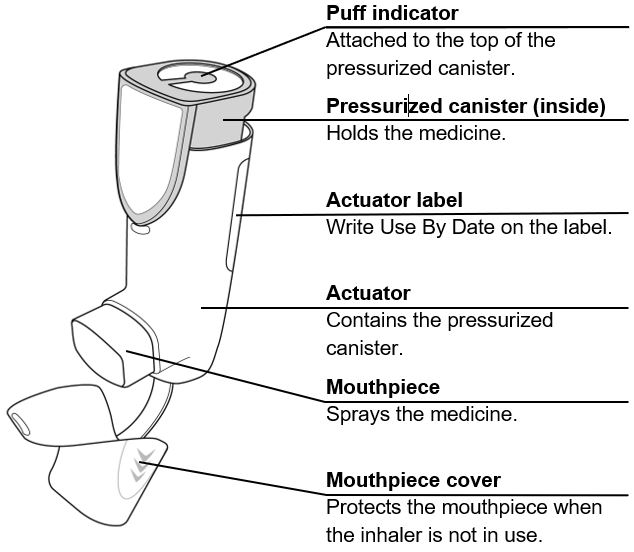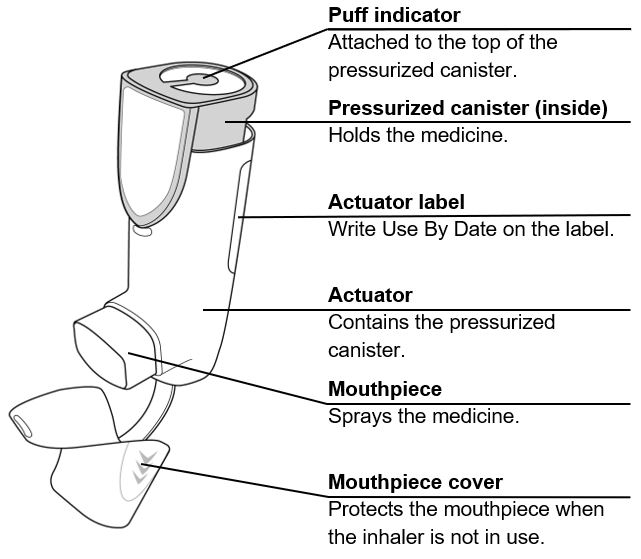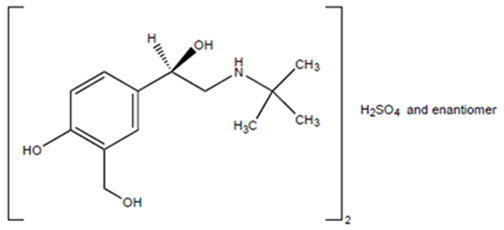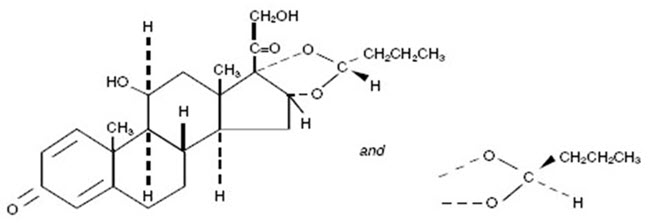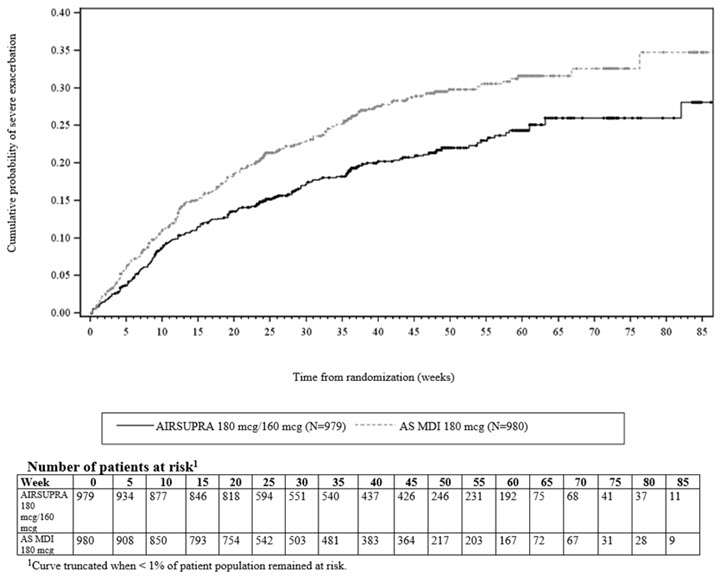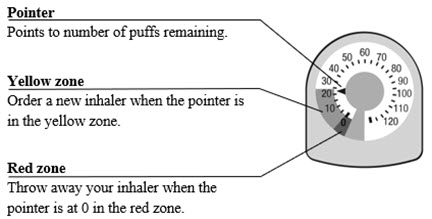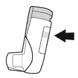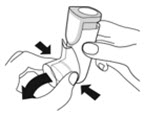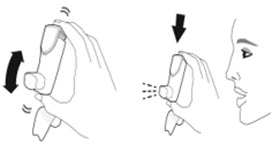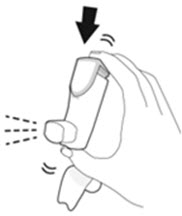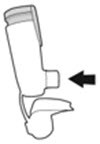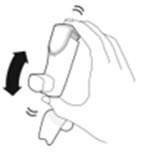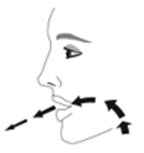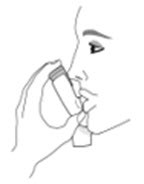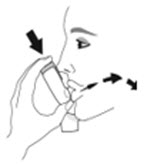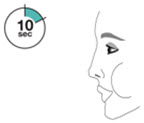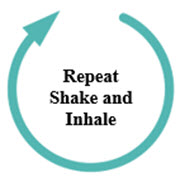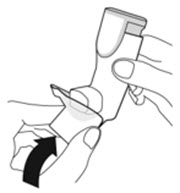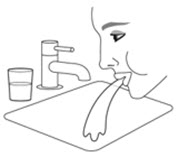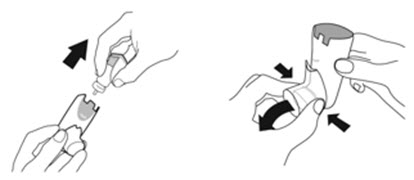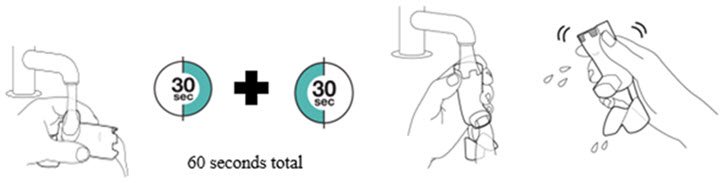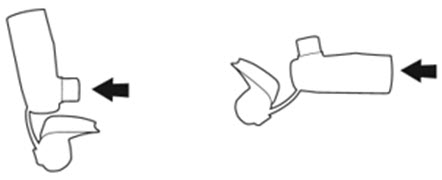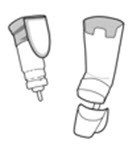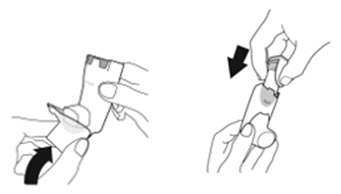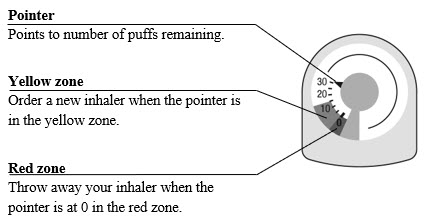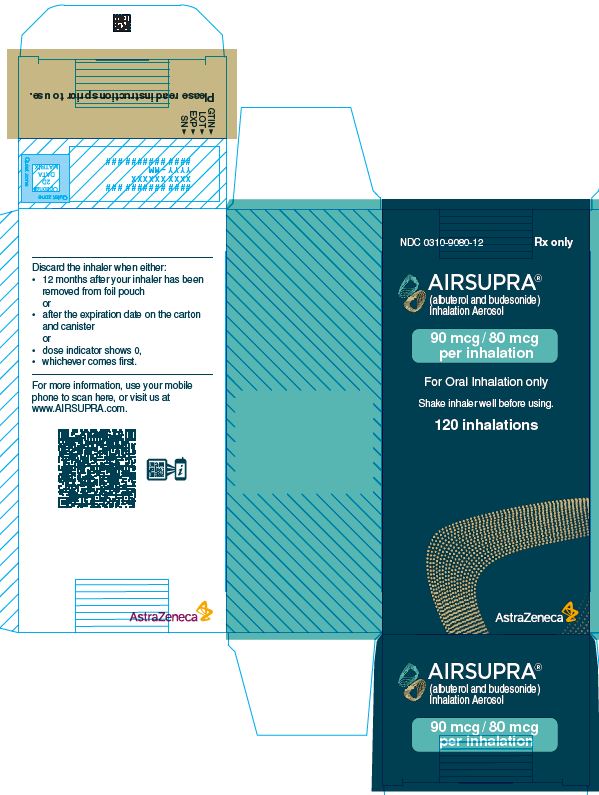 DRUG LABEL: AIRSUPRA
NDC: 0310-9080 | Form: AEROSOL, METERED
Manufacturer: AstraZeneca Pharmaceuticals LP
Category: prescription | Type: HUMAN PRESCRIPTION DRUG LABEL
Date: 20250918

ACTIVE INGREDIENTS: ALBUTEROL SULFATE 90 ug/1 1; BUDESONIDE 80 ug/1 1
INACTIVE INGREDIENTS: 1,2-DISTEAROYL-SN-GLYCERO-3-PHOSPHOCHOLINE; CALCIUM CHLORIDE; NORFLURANE

HIGHLIGHTS OF PRESCRIBING INFORMATION

These highlights do not include all the information needed to use AIRSUPRA® safely and effectively. See full prescribing information for AIRSUPRA.
AIRSUPRA (albuterol and budesonide) inhalation aerosol, for oral inhalation use
Initial U.S. Approval: 2023

1 INDICATIONS AND USAGE

AIRSUPRA is a combination of albuterol, a beta2-adrenergic agonist and budesonide, a corticosteroid, indicated for the as-needed treatment or prevention of bronchoconstriction and to reduce the risk of exacerbations in patients with asthma 18 years of age and older. (1)

2 DOSAGE AND ADMINISTRATION

- Recommended Dosage: AIRSUPRA 180 mcg/160 mcg (administered as 2 actuations of albuterol/budesonide 90 mcg/80 mcg) by oral inhalation as needed for asthma symptoms. (2.1)
- Do not take more than 6 doses (12 inhalations) in a 24-hour period. (2.1)
- Prime inhaler prior to first use. Re-prime when inhaler has not been used for more than 7 days, is dropped, or after cleaning. (2.2)
- Discard when the dose counter displays 0. (2.3)

3 DOSAGE FORMS AND STRENGTHS

Inhalation aerosol: Pressurized metered dose inhaler that delivers a combination of albuterol 90 mcg and budesonide 80 mcg per actuation. (3)

4 CONTRAINDICATIONS

Hypersensitivity to albuterol, budesonide, or to any of the excipients. (4)

5 WARNINGS AND PRECAUTIONS

- If symptoms continue after using AIRSUPRA, this may be a marker of destabilization of asthma and requires reevaluation of treatment. (5.1)
- If paradoxical bronchospasm occurs, discontinue AIRSUPRA immediately and institute alternative therapy. (5.2)
- Cardiovascular effects may occur. Use with caution in patients sensitive to sympathomimetic drugs and patients with cardiovascular disorders. (5.3)
- Excessive use may be fatal. Do not exceed maximum recommended dosage. (5.4)
- Hypersensitivity reactions may occur. Discontinue AIRSUPRA immediately. (5.5)
- Use with caution in patients with convulsive disorders, hyperthyroidism, diabetes mellitus, and ketoacidosis. (5.6)
- Hypokalemia may occur. (5.7)
- Potential worsening of infections (e.g., existing tuberculosis; fungal, bacterial, viral, or parasitic infections; or ocular herpes simplex). Use with caution in patients with these infections. More serious or even fatal course of chickenpox or measles can occur in susceptible patients. (5.8)
- Oropharyngeal candidiasis may occur. Advise patients to rinse mouth with water, if available, without swallowing after use. Monitor patients periodically. (5.9)
- Hypercorticism and adrenal suppression may occur with very high dosages in susceptible individuals. If such changes occur, consider appropriate therapy. (5.10)
- Monitor patients with major risk factors for decreased bone mineral content. (5.11)
- Glaucoma and cataracts may occur. Consider referral to an ophthalmologist in patients who develop ocular symptoms. (5.12)

6 ADVERSE REACTIONS

Most common adverse reactions (incidence ≥ 1%) are headache, oral candidiasis, cough, dysphonia. (6.1)

To report SUSPECTED ADVERSE REACTIONS, contact AstraZeneca at 1-800-236-9933 or FDA at 1-800-FDA-1088 or www.fda.gov/medwatch.

7 DRUG INTERACTIONS

- Strong cytochrome P450 3A4 inhibitors (e.g. ritonavir): Use with caution. May cause systemic corticosteroid effects. (7.1)
- Other short-acting bronchodilators: Use judiciously with other short-acting beta agonists. (7.2)
- Beta blockers: May decrease effectiveness of AIRSUPRA and produce severe bronchospasm. When there are no acceptable alternatives to the use of beta-adrenergic-blocking agents, consider cardioselective beta-blockers and use with caution. (7.3)
- Diuretics, or non-potassium-sparing diuretics: May potentiate hypokalemia or ECG changes. Consider monitoring potassium levels with concomitant use. (7.4)
- Digoxin: May decrease serum digoxin levels. Carefully evaluate digoxin levels with concomitant use. (7.5)
- Monoamine oxidase inhibitors (MAOI) and tricyclic antidepressants: Use AIRSUPRA with extreme caution with concomitant use. (7.6)

8 USE IN SPECIFIC POPULATIONS

Hepatic impairment: Budesonide systemic exposure may increase in patients with severe hepatic impairment. Monitor patients with hepatic disease. (8.6)

FULL PRESCRIBING INFORMATION

1 INDICATIONS AND USAGE

AIRSUPRA is indicated for the as-needed treatment or prevention of bronchoconstriction and to reduce the risk of exacerbations in patients with asthma 18 years of age and older.

2 DOSAGE AND ADMINISTRATION

2.1 Recommended Dosage and Administration

The recommended dosage of AIRSUPRA is albuterol 180 mcg and budesonide 160 mcg (administered as 2 actuations of AIRSUPRA [albuterol/budesonide 90 mcg/80 mcg]) as needed for asthma symptoms by oral inhalation. Do not take more than 6 doses (12 inhalations) in a 24-hour period [see Warnings and Precautions (5.4)].

2.2 Priming Before Use

- Priming AIRSUPRA is essential to ensure appropriate drug content in each actuation. Prime AIRSUPRA before using for the first time. To prime AIRSUPRA, release 4 sprays into the air away from the face, shaking well before each spray.
- AIRSUPRA must be re-primed when the inhaler has not been used for more than 7 days, is dropped, or after cleaning. To re-prime AIRSUPRA, release 2 sprays into the air away from the face, shaking well before each spray.

2.3 Dose Counter

The canister has an attached dose indicator (also known as puff indicator) which indicates how many inhalations (puffs) remain. The dose indicator pointer will move after every actuation. The pointer will show the number of inhalations remaining in the canister. When nearing the end of the usable inhalations, the color behind the number in the dose indicator display window changes to yellow. AIRSUPRA should be discarded when the pointer reaches zero.

3 DOSAGE FORMS AND STRENGTHS

Inhalation aerosol: a pressurized metered dose inhaler (a pressurized canister with an attached dose indicator, supplied with a white plastic actuator with a frosted clear plastic dust cap) that delivers a combination of albuterol 90 mcg and budesonide 80 mcg per actuation.

4 CONTRAINDICATIONS

AIRSUPRA is contraindicated in patients with a history of hypersensitivity to albuterol, budesonide, or any of the excipients [see Warnings and Precautions (5.5), Description (11)].

5 WARNINGS AND PRECAUTIONS

5.1 Deterioration of Asthma

Asthma may deteriorate acutely over a period of hours or chronically over several days or longer. If the patient continues to experience symptoms after using AIRSUPRA or requires more doses of AIRSUPRA than usual, this may be a marker of destabilization of asthma and requires evaluation of the patient and their treatment regimen.

5.2 Paradoxical Bronchospasm

AIRSUPRA can produce paradoxical bronchospasm, which may be life threatening. If paradoxical bronchospasm occurs following dosing with AIRSUPRA, it should be discontinued immediately, and alternative therapy should be instituted. It should be recognized that paradoxical bronchospasm, when associated with inhaled formulations, frequently occurs with the first use of a new canister.

5.3 Cardiovascular Effects

AIRSUPRA, like other drugs containing beta2-adrenergic agonists, can produce clinically significant cardiovascular effects in some patients as measured by increases in pulse rate, blood pressure, and/or other symptoms. If such effects occur, AIRSUPRA may need to be discontinued. In addition, beta-agonists have been reported to produce electrocardiogram (ECG) changes, such as flattening of the T wave, prolongation of the QTc interval, and ST-segment depression. The clinical significance of these findings is unknown. Therefore, AIRSUPRA, like all sympathomimetic amines, should be used with caution in patients with cardiovascular disorders, especially coronary insufficiency, cardiac arrhythmias, and hypertension.

5.4 Do Not Exceed Recommended Dosage

As with other inhaled drugs containing beta-adrenergic agents, AIRSUPRA should not be used more than the maximum daily dose [see Dosage and Administration (2.1)], as an overdose may result. Clinically significant cardiovascular effects and fatalities have been reported in association with excessive use of inhaled sympathomimetic drugs.

5.5 Hypersensitivity Reactions, Including Anaphylaxis

Hypersensitivity reactions can occur after administration of albuterol sulfate and budesonide, components of AIRSUPRA, as demonstrated by cases of anaphylaxis, angioedema, bronchospasm, oropharyngeal edema, rash, and urticaria. Discontinue AIRSUPRA if such reactions occur [see Contraindications (4)].

5.6 Risk of Sympathomimetic Amines with Certain Coexisting Conditions

AIRSUPRA, like all therapies containing sympathomimetic amines, should be used with caution in patients with convulsive disorders, hyperthyroidism, or diabetes mellitus and in patients who are unusually responsive to sympathomimetic amines. Large doses of intravenous albuterol have been reported to aggravate preexisting diabetes mellitus and ketoacidosis.

5.7 Hypokalemia

Beta-adrenergic agonist medicines may produce significant hypokalemia in some patients, possibly through intracellular shunting, which has the potential to produce adverse cardiovascular effects [see Warnings and Precautions (5.3), Clinical Pharmacology (12.1)]. The decrease in serum potassium is usually transient, not requiring supplementation.

5.8 Immunosuppression and Risk of Infections

Patients who are using drugs that suppress the immune system are more susceptible to infection. Chicken pox and measles, for example, can have a more serious or even fatal course in susceptible patients using corticosteroids. In patients who have not had these diseases or been properly immunized, particular care should be taken to avoid exposure. How the dose, route, and duration of corticosteroid administration affects the risk of developing a disseminated infection is not known. The contribution of the underlying disease and/or prior corticosteroid treatment to the risk is also not known. If a patient is exposed to chicken pox, prophylaxis with varicella zoster immune globulin (VZIG) may be indicated. If exposed to measles, prophylaxis with pooled intramuscular immunoglobulin (IG) may be indicated (see the respective Prescribing Information for VZIG and IG). If chicken pox develops, treatment with antiviral agents may be considered.

Inhaled corticosteroids should be used with caution, if at all, in patients with active or quiescent tuberculosis infection of the respiratory tract; untreated systemic fungal, bacterial, viral, or parasitic infections; or ocular herpes simplex.

5.9 Oropharyngeal Candidiasis

AIRSUPRA contains budesonide, an inhaled corticosteroid (ICS). Localized infections of the mouth and pharynx with Candida albicans have occurred in patients treated with ICS agents. Monitor patients periodically. When such an infection develops, it should be treated with appropriate local or systemic (i.e., oral) antifungal therapy while treatment with AIRSUPRA continues. In some cases, therapy with AIRSUPRA may need to be interrupted. Advise the patient to rinse his/her mouth with water, if available, without swallowing following administration of AIRSUPRA to help reduce the risk of oropharyngeal candidiasis.

5.10 Hypercorticism and Adrenal Suppression

Budesonide, a component of AIRSUPRA, will often help control asthma symptoms with less suppression of hypothalamic-pituitary-adrenal (HPA) function than therapeutically equivalent oral doses of prednisone. Since budesonide is absorbed into the circulation and can be systemically active at higher doses, the beneficial effects of AIRSUPRA in minimizing HPA dysfunction may be expected only when recommended dosages are not exceeded. Since individual sensitivity to effects on cortisol production exists, physicians should consider this information when prescribing AIRSUPRA.

Because of the possibility of systemic absorption of ICS, patients treated with AIRSUPRA should be observed carefully for any evidence of systemic corticosteroid effects. Particular care should be taken in observing patients postoperatively or during periods of stress for evidence of inadequate adrenal response.

It is possible that systemic corticosteroid effects such as hypercorticism and adrenal suppression (including adrenal crisis) may appear in a small number of patients who are sensitive to these effects. If such effects occur, appropriate therapy should be initiated as needed.

5.11 Reduction in Bone Mineral Density

Decreases in bone mineral density (BMD) have been observed with long-term administration of products containing ICS. The clinical significance of small changes in BMD with regard to long-term consequences such as fracture is unknown. Patients with major risk factors for decreased bone mineral content, such as prolonged immobilization, family history of osteoporosis, post-menopausal status, tobacco use, advanced age, poor nutrition, or chronic use of drugs that can reduce bone mass (e.g., anticonvulsants, oral corticosteroids) should be monitored and treated with established standards of care.

5.12 Glaucoma and Cataracts

Glaucoma, increased intraocular pressure, and cataracts have been reported following the long-term administration of ICS, including budesonide, a component of AIRSUPRA. Consider referral to an ophthalmologist in patients who develop ocular symptoms.

5.13 Drug Interactions with Strong Cytochrome P450 3A4 Inhibitors

Caution should be exercised when considering the co-administration of AIRSUPRA with long-term ketoconazole and other known strong CYP3A4 inhibitors (e.g., ritonavir, atazanavir, clarithromycin, indinavir, itraconazole, nefazodone, nelfinavir, saquinavir, telithromycin) because adverse effects related to increased systemic exposure to budesonide may occur [see Drug Interactions (7.1), Clinical Pharmacology (12.3)].

5.14 Effects on Growth in Pediatric Patients

Orally inhaled corticosteroids, including budesonide, may cause a reduction in growth velocity when administered to pediatric patients. The safety and effectiveness of AIRSUPRA have not been established in pediatric patients, and AIRSUPRA is not indicated for use in this population [see Use in Specific Populations (8.4)].

6 ADVERSE REACTIONS

The following clinically significant adverse reactions are described elsewhere in labeling:

- Deterioration of Asthma [see Warnings and Precautions (5.1)]
- Paradoxical Bronchospasm [see Warnings and Precautions (5.2)]
- Cardiovascular Effects [see Warnings and Precautions (5.3)]
- Hypersensitivity Reactions, including Anaphylaxis [see Warnings and Precautions (5.5)]
- Hypokalemia [see Warnings and Precautions (5.7)]
- Immunosuppression and Risk of Infections [see Warnings and Precautions (5.8)]
- Oropharyngeal Candidiasis [see Warnings and Precautions (5.9)]
- Hypercorticism and Adrenal Suppression [see Warnings and Precautions (5.10)]
- Reduction in Bone Mineral Density [see Warnings and Precautions (5.11)]
- Glaucoma and Cataracts [see Warnings and Precautions (5.12)]
- Effects on Growth in Pediatric Patients [see Warnings and Precautions (5.14)]

6.1 Clinical Trials Experience

Because clinical trials are conducted under widely varying conditions, adverse reaction rates observed in the clinical trials of a drug cannot be directly compared to rates in the clinical trials of another drug and may not reflect the rates observed in practice.

The safety of AIRSUPRA is based on data from 3 trials: MANDALA, DENALI and BATURA [see Clinical Studies (14)]. All reported safety data is based on patients who received AIRSUPRA 180 mcg/160 mcg. While patients 12 to 17 years of age were included in these trials, AIRSUPRA is not approved in this age group [see Use in Specific Populations (8.4)].

In MANDALA, AIRSUPRA 180 mcg/160 mcg was administered as needed in patients with asthma who were receiving medium to high dose ICS or low to high dose ICS/LABA, with or without another controller medicine as maintenance therapy. A total of 1015 patients 12 to 84 years of age (mean age: 51 years) received at least one dose of AIRSUPRA and participated in the study for a mean duration of 310 days. Of these, 905 patients were exposed for at least 24 weeks and 323 patients had exposure for at least 1 year. The mean daily use was 2.6 actuations. On the majority of study days, patients used 2 or less actuations; more than 8 actuations were used on less than 2% of study days.

The incidence of common adverse reactions in MANDALA is described in Table 1.

Table 1 Summary of Adverse Reactions with AIRSUPRA Reported in ≥ 1% of Patients (MANDALA)
Adverse Reaction | AIRSUPRA 180 mcg/160 mcg N = 1015 (%) | AS MDI^1 180 mcg N = 1015 (%)
Headache | 44 (4.3) | 50 (4.9)
Oral candidiasis^2 | 13 (1.3) | 5 (0.5)
Cough | 10 (1.0) | 11 (1.1)
^1 Albuterol Metered Dose Inhaler = AS MDI
^2 Oral candidiasis also includes those reactions reported under the preferred term oropharyngeal candidiasis.

The safety profile of AIRSUPRA in MANDALA was similar to that observed with AS MDI, irrespective of background ICS dose.

In DENALI, AIRSUPRA 180 mcg/160 mcg was administered 4 times a day for 12 weeks in patients with asthma who were previously treated with as-needed short-acting beta2-agonists (SABA) alone or with low-dose ICS maintenance therapy plus as-needed SABA. A total of 197 patients 13 to 81 years of age (mean age: 50 years) received at least one dose of AIRSUPRA. The adverse reactions profile was similar to MANDALA except for the following adverse reactions for AIRSUPRA with an incidence ≥ 1.0% that exceeded the incidence in MANDALA: headache (5.1%), dysphonia (2.0%), and oral/oropharyngeal candidiasis (1.5%), compared to headache (7.1%), dysphonia (0%), and oral/oropharyngeal candidiasis (0%) in the placebo arm.

In BATURA, AIRSUPRA 180 mcg/160 mcg was administered as needed for 12 to 52 weeks in patients with asthma who were previously treated with as-needed SABA alone, or as-needed SABA plus background maintenance of either low-dose ICS or leukotriene receptor antagonist (LTRA). The 26% of patients on background ICS or LTRA were instructed to continue these treatments throughout the study period. A total of 1209 patients 12 to 95 years of age (mean age: 43 years) received at least one dose of AIRSUPRA and participated in the study for a mean duration of 259 days. Of them, 1109 patients were exposed for at least 12 weeks and 258 patients were exposed for at least 1 year. The mean daily use was 1.5 actuations for AIRSUPRA and 1.8 actuations for AS MDI 180 mcg. On the majority of study days, patients used 2 or less actuations of AIRSUPRA or AS MDI 180 mcg; more than 8 actuations were used on 2% of study days for patients on AIRSUPRA and 4% of study days for patients on AS MDI 180 mcg. The safety profile of AIRSUPRA in BATURA was similar to that in MANDALA.

6.2 Postmarketing Experience

The following adverse reactions have been identified during post-approval use of budesonide or albuterol. Because these reactions are reported voluntarily from a population of uncertain size, it is not always possible to reliably estimate their frequency or establish a causal relationship to drug exposure.

Cardiovascular disorders: myocardial ischemia, tremor, tachycardia, palpitations, extrasystoles, arrhythmias (including atrial fibrillation, supraventricular tachycardia), syncope, hypertension, peripheral vasodilatation

Endocrine disorders: signs or symptoms of systemic glucocorticosteroid effect (including hypofunction of the adrenal gland and reduction of growth rate)

Eye disorders: cataracts, glaucoma, increased intraocular pressure

Immune system disorders: immediate and delayed hypersensitivity reactions (including anaphylactic reaction, angioedema, bronchospasm, rash, contact dermatitis and urticaria)

General disorders: fever, weight gain, taste perversion, flu syndrome

Gastrointestinal disorders: nausea, vomiting, dyspepsia, diarrhea

Infections: sinusitis, pharyngitis, respiratory tract infection, nasopharyngitis, gastroenteritis, otitis media, laryngitis

Metabolic disorders: hypokalemia, metabolic acidosis

Musculoskeletal disorders: hypertonia, musculoskeletal pain, myalgia, asthenia, arthralgia, muscle cramps, fracture

Neurological or psychiatric system disorders: migraine, dizziness, central nervous system stimulation, insomnia, hyperactivity, psychiatric symptoms (including psychosis, depression, aggressive reactions, irritability, nervousness, restlessness, behavioral disturbances and anxiety)

Respiratory, thoracic, and mediastinal disorders: rhinitis, nasal congestion, throat irritation, oropharyngeal edema, upper respiratory inflammation, drying or irritation of the oropharynx

Skin and subcutaneous tissue disorders: skin bruising, ecchymosis

7 DRUG INTERACTIONS

No formal drug interaction studies have been performed with AIRSUPRA.

7.1 Inhibitors of Cytochrome P450 3A4

The main route of metabolism of corticosteroids, including budesonide, a component of AIRSUPRA, is via cytochrome P450 (CYP) isoenzyme 3A4 (CYP3A4). After oral administration of ketoconazole, a strong inhibitor of CYP3A4, the mean plasma concentration of orally administered budesonide increased. Concomitant administration of a CYP3A4 inhibitor may inhibit the metabolism of, and increase the systemic exposure to, budesonide. Caution should be exercised when considering the co-administration of AIRSUPRA with long-term ketoconazole and other known strong CYP3A4 inhibitors (e.g., ritonavir, atazanavir, clarithromycin, indinavir, itraconazole, nefazodone, nelfinavir, saquinavir, telithromycin) [see Warnings and Precautions (5.11)].

7.2 Use with Other Short-Acting Bronchodilators

AIRSUPRA contains the short-acting beta-agonist, albuterol. Therefore, concomitant use of additional beta-agonists with AIRSUPRA should be used judiciously to prevent beta-agonist overdose.

7.3 Beta-Blockers

Beta-adrenergic receptor blocking agents not only block the pulmonary effect of beta-agonists, such as albuterol, a component of AIRSUPRA, but may also produce severe bronchospasm in patients with asthma. Therefore, patients with asthma should not normally be treated with beta-blockers. However, under certain circumstances, e.g., as prophylaxis after myocardial infarction, there may be no acceptable alternatives to the use of beta-adrenergic-blocking agents in these patients. In this setting, consider cardioselective beta-blockers, although they should be administered with caution.

7.4 Diuretics

The ECG changes and/or hypokalemia which may result from the administration of non-potassium-sparing diuretics (such as loop or thiazide diuretics) can be acutely worsened by beta-agonists, especially when the recommended dose of the beta-agonist is exceeded. Although the clinical significance of these effects is not known, caution is advised in the coadministration of AIRSUPRA with non-potassium-sparing diuretics. Consider monitoring potassium levels.

7.5 Digoxin

Mean decreases of 16% and 22% in serum digoxin levels were demonstrated after single-dose intravenous and oral administration of albuterol, respectively, to normal volunteers who had received digoxin for 10 days. The clinical significance of these findings for patients with obstructive airway disease who are receiving albuterol and digoxin on a chronic basis is unclear. Nevertheless, it would be prudent to carefully evaluate the serum digoxin levels in patients who are currently receiving digoxin and AIRSUPRA.

7.6 Monoamine Oxidase Inhibitors or Tricyclic Antidepressants

AIRSUPRA should be administered with extreme caution to patients being treated with monoamine oxidase inhibitors or tricyclic antidepressants, or within 2 weeks of discontinuation of such agents, because the action of albuterol on the cardiovascular system may be potentiated.

8 USE IN SPECIFIC POPULATIONS

8.1 Pregnancy

Pregnancy Exposure Registry

There is a pregnancy exposure registry that monitors pregnancy outcomes in women exposed to asthma medications during pregnancy. For more information, contact the MotherToBaby Pregnancy Studies conducted by the Organization of Teratology Information Specialists at 1-877-311-8972 or visit http://mothertobaby.org/pregnancy-studies/.

Risk Summary

Available data from published case series, epidemiological studies and reviews with budesonide use in pregnant women have not identified a drug-related risk of major birth defects, miscarriage or other adverse maternal or fetal outcomes. Available data from epidemiological studies and postmarketing case reports of pregnancy outcomes following inhaled albuterol use do not consistently demonstrate a risk of major birth defects or miscarriage. The available epidemiological studies have methodologic limitations, including inconsistent comparator groups, definitions of outcomes, and assessment of disease impact. There are risks to the mother and fetus associated with asthma in pregnancy (see Clinical Considerations). Animal reproduction studies have not been conducted with AIRSUPRA, however, animal studies are available with its individual components, albuterol and budesonide.

Administration of albuterol to mice and rabbits during the period of organogenesis revealed evidence of adverse developmental outcomes (cleft palate in mice, delayed ossification in rabbits) at less than maximum recommended human daily inhalation dose (MRHDID) (see Data).

In animal reproduction studies, budesonide, administered by the subcutaneous route, caused structural abnormalities, was embryocidal, and reduced fetal weights in rats and rabbits at less than the MRHDID in adults, but these effects were not seen in rats that received inhaled doses approximately 2.5 times the MRHDID in adults (see Data). Experience with oral corticosteroids suggests that rodents are more prone to structural abnormalities from corticosteroid exposure than humans.

The background risk of major birth defects and miscarriage of the indicated populations is unknown. All pregnancies have a background risk of birth defect, loss, or other adverse outcomes. In the U.S. general population, the estimated background risk of major birth defects and miscarriage in clinically recognized pregnancies is 2% to 4% and 15% to 20%, respectively.

Clinical Considerations

Disease-Associated Maternal and/or Embryo/Fetal risk

In women with poorly or moderately controlled asthma, there is an increased risk of several perinatal adverse outcomes such as preeclampsia in the mother and prematurity, low birth weight, and small for gestational age in the neonate. Pregnant women with asthma should be closely monitored and medication adjusted as necessary to maintain optimal asthma control.

Labor or Delivery

Because of the potential for beta-agonist interference with uterine contractility, use of AIRSUPRA during labor should be restricted to those patients in whom the benefits clearly outweigh the risk. AIRSUPRA has not been approved for the management of pre-term labor. Serious adverse reactions, including pulmonary edema, have been reported during or following treatment of premature labor with beta2-agonists, including albuterol.

Data

Animal Data

Albuterol
In a study in pregnant mice, subcutaneously administered albuterol sulfate produced cleft palate formation in 5 of 111 (4.5%) fetuses at an exposure less than the MRHDID in adults (on a mg/m^2 basis at a maternal dose of 0.25 mg/kg) and in 10 of 108 (9.3%) fetuses at approximately 9 times the MRHDID in adults (on a mg/m^2 basis at a maternal dose of 2.5 mg/kg). Cleft palate also occurred in 22 of 72 (30.5%) fetuses from females treated subcutaneously with isoproterenol, another beta2-agonist.

In a study in pregnant rabbits, orally administered albuterol sulfate produced cranioschisis in 7 of 19 fetuses (37%) at approximately 750 times the MRHDID in adults (on a mg/m^2 basis at a maternal dose of 50 mg/kg).

In a study in pregnant rabbits, an albuterol/HFA-134a formulation administered by inhalation produced enlargement of the frontal portion of the fetal fontanelles at approximately one third of the MRHDID on a mg/m^2 basis.

A study in which pregnant rats were dosed with radiolabeled albuterol sulfate demonstrated that drug-related material is transferred from the maternal circulation to the fetus.

Budesonide
In a fertility and reproduction study, male rats were subcutaneously dosed with budesonide for 9 weeks and females for 2 weeks prior to pairing and throughout the mating period. Females were dosed up until weaning of their offspring. Budesonide caused a decrease in prenatal viability and viability in the pups at birth and during lactation, along with a decrease in maternal body-weight gain, at doses 0.2 times the MRHDID in adults (on a mcg/m^2 basis at maternal subcutaneous doses of 20 mcg/kg/day and above). No such effects were noted at a dose 0.05 times the MRHDID in adults (on a mcg/m^2 basis at a maternal subcutaneous dose of 5 mcg/kg/day).

In an embryo-fetal development study in pregnant rabbits dosed during the period of organogenesis from gestation days 6-18, budesonide produced fetal loss, decreased fetal weight, and skeletal abnormalities at doses 0.5 times the MRHDID in adults (on a mcg/m^2 basis at a maternal subcutaneous dose of 25 mcg/kg/day). In an embryo-fetal development study in pregnant rats dosed during the period of organogenesis from gestation days 6-15, budesonide produced similar adverse fetal effects at doses approximately 5 times the MRHDID in adults (on a mcg/m^2 basis at a maternal subcutaneous dose of 500 mcg/kg/day). In another embryo-fetal development study in pregnant rats, no structural abnormalities or embryocidal effects were seen at doses approximately 2.5 times the MRHDID in adults (on a mcg/m^2 basis at maternal inhalation doses up to 250 mcg/kg/day).

In a peri- and post-natal development study, rats were dosed from gestation day 15 to postpartum day 21. Budesonide had no effects on delivery but did have an effect on growth and development of offspring. Offspring survival was reduced and surviving offspring had decreased mean body weights at birth and during lactation at doses 0.2 times the MRHDID in adults and higher (on a mcg/m^2 basis at maternal subcutaneous doses of 20 mcg/kg/day and higher). These findings occurred in the presence of maternal toxicity.

8.2 Lactation

Risk Summary

There are no available data on the effects of AIRSUPRA on the breastfed child or on milk production.

There are no available data on the presence of albuterol in human milk, the effects on the breastfed child, or the effects on milk production. However, plasma levels of albuterol after inhaled therapeutic doses are low in humans, and if present in breast milk, are likely to be correspondingly low.

Budesonide, like other inhaled corticosteroids, is present in human milk (see Data).

The developmental and health benefits of breastfeeding should be considered along with the mother’s clinical need for AIRSUPRA and any potential adverse effects on the breastfed child from AIRSUPRA or from the underlying maternal condition.

Data

One published study reports that budesonide is present in human milk following maternal inhalation of budesonide, which resulted in infant doses approximately 0.3% to 1% of the maternal weight-adjusted dosage and a milk to plasma ratio was approximately 0.5. Budesonide was not detected in plasma, and no adverse events were noted in the breastfed infants following maternal use of inhaled budesonide.

For AIRSUPRA, the dose of budesonide available to the infant in breast milk, as a percentage of the maternal dose, would be expected to be similar.

Budesonide levels in plasma samples obtained from five infants at about 90 minutes after breastfeeding (and about 140 minutes after drug administration to the mother) were below quantifiable levels (< 0.02 nmol/L in four infants and < 0.04 nmol/L in one infant).

8.4 Pediatric Use

The safety and effectiveness of AIRSUPRA have not been established in pediatric patients. A limited number of pediatric patients were enrolled in the efficacy trials MANDALA (4 to 17 years of age) and BATURA (12 to 17 years of age) to evaluate AIRSUPRA to reduce the risk of severe asthma exacerbations. The primary efficacy endpoint was time to first severe asthma exacerbation. MANDALA enrolled patients with asthma who were receiving medium to high dose ICS or low to high dose ICS/LABA, with or without another controller medicine as maintenance therapy. In MANDALA, there were 9 patients with severe exacerbation events in 34 patients 12 to 17 years of age treated with AIRSUPRA 180 mcg/160 mcg and 7 patients with severe exacerbation events in 34 patients treated with albuterol (AS MDI) [HR 1.44 (0.54, 3.87)]. There were 11 patients with severe exacerbation events in 41 patients 4 to 11 years of age treated with albuterol/budesonide (AS-BD MDI) 180 mcg/80 mcg and 10 in the 42 patients 4 to 11 years of age treated with AS MDI [HR: 1.09 (0.46, 2.56)]. BATURA enrolled patients with asthma who were previously treated with as-needed SABA alone, or as-needed SABA plus background maintenance of either low-dose ICS or LTRA. In the BATURA trial, 1 patient had a severe exacerbation event in 29 patients treated with AIRSUPRA 180 mcg/160 mcg and 1 patient with severe exacerbation events in 39 patients treated with AS MDI. These data are inadequate to make a determination regarding the safety or effectiveness of AIRSUPRA or AS-BD 180 mcg/80 mcg in pediatric patients 4 to 17 years of age [see Clinical Studies (14)].

Controlled clinical studies have shown that ICS agents, including budesonide, one of the components of AIRSUPRA, may cause a reduction in growth velocity in pediatric patients. The effects of long-term treatment of pediatric patients with ICS on final adult height are not known [see Warnings and Precautions (5.14)].

8.5 Geriatric Use

There were 921 patients 65 years of age and older in the clinical studies for asthma [see Clinical Studies (14)]. Of the total number of AIRSUPRA-treated patients in these studies, 311 (13%) were 65 years of age and older, while 52 (2%) were 75 years of age and older. In general, no differences in safety or effectiveness were observed between these patients and younger patients, and other reported clinical experience has not identified differences in responses between the elderly and younger patients, but greater sensitivity of some older individuals cannot be ruled out.

As with other products containing beta2-agonists, special caution should be observed when using AIRSUPRA in geriatric patients who have concomitant cardiovascular disease that could be adversely affected by this class of drug.

All beta2-adrenergic agonists, including albuterol, are known to be substantially excreted by the kidney, and the risk of toxic reactions may be greater in patients with impaired renal function. Because geriatric patients are more likely to have decreased renal function, care should be taken when dosing, and it may be useful to monitor renal function.

8.6 Hepatic Impairment

Formal pharmacokinetic studies using AIRSUPRA have not been conducted in patients with hepatic impairment. However, since budesonide is predominantly cleared by hepatic metabolism, impairment of liver function may lead to accumulation of budesonide in the plasma. Therefore, patients with hepatic disease should be closely monitored.

8.7 Renal Impairment

Formal pharmacokinetic studies using AIRSUPRA have not been conducted in patients with renal impairment.

10 OVERDOSAGE

AIRSUPRA contains both albuterol and budesonide; therefore, the risks associated with overdosage for the individual components described below apply to AIRSUPRA.

Albuterol

The expected symptoms with overdosage are those of excessive beta-adrenergic stimulation and/or occurrence or exaggeration of any of the symptoms of beta-adrenergic stimulation (e.g., seizures, angina, hypertension or hypotension, tachycardia with rates up to 200 beats/minute, arrhythmias, nervousness, headache, tremor, muscle cramps, dry mouth, palpitation, nausea, dizziness, fatigue, malaise, insomnia, hyperglycemia, and metabolic acidosis).

Hypokalemia may also occur. As with all sympathomimetic medications, cardiac arrest and even death may be associated with abuse of AIRSUPRA.

Treatment consists of discontinuation of AIRSUPRA together with appropriate symptomatic therapy. The judicious use of a cardioselective beta-receptor blocker may be considered, bearing in mind that such medication can produce bronchospasm. There is insufficient evidence to determine if dialysis is beneficial for overdosage of AIRSUPRA.

Budesonide

If used at excessive doses for prolonged periods, systemic corticosteroid effects such as hypercorticism may occur [see Warnings and Precautions (5.10)].

11 DESCRIPTION

AIRSUPRA (albuterol and budesonide) Inhalation Aerosol is a pressurized metered dose inhaler containing a combination of micronized albuterol sulfate, a relatively selective, short-acting beta2-adrenergic agonist and micronized budesonide, a corticosteroid, for oral inhalation.

Albuterol sulfate is the official generic name in the United States. The World Health Organization recommended name for the drug is salbutamol sulfate. Albuterol sulfate has the following chemical name: USP racemic α^1 [(tert-Butylamino)methyl]-4-hydroxy-m-xylene-α,α'-diol sulfate (2:1) (salt). The empirical formula is (C13H21NO3)2•H2SO4, and the molecular weight is 576.7. Its structural formula is:

Albuterol sulfate is a white to off-white powder that is freely soluble in water, slightly soluble in alcohol and in ether, and practically insoluble in chloroform. It has a LogP of 0.44 at physiological pH. Albuterol has one chiral center and exists as a 1:1 racemic mixture.

Budesonide is a corticosteroid designated chemically as (RS)-11β, 16α, 17,21-Tetrahydroxypregna-1,4-diene-3,20-dione cyclic 16,17-acetal with butyraldehyde. Budesonide is provided as a mixture of two epimers (22R and 22S). The empirical formula of budesonide is C25H34O6 and its molecular weight is 430.5. Its structural formula is:

Budesonide is a white to off-white powder that is practically insoluble in water and in heptane, sparingly soluble in ethanol, and freely soluble in chloroform. Its partition coefficient between octanol and water at pH 7.4 is 1.6 x 10^3.

AIRSUPRA is formulated as a hydrofluoroalkane (HFA-134a) propelled pressurized metered dose inhaler containing 120 inhalations. The canister has an attached dose indicator and is supplied with a white plastic actuator with a frosted clear plastic dust cap tethered to it.

After priming, each actuation of AIRSUPRA 90 mcg/80 mcg meters 99 mcg of albuterol and 88 mcg of budesonide from the valve which delivers 90 mcg of albuterol (equivalent to 108 mcg of albuterol sulfate) and 80 mcg of budesonide from the actuator. The actual amount of drug delivered to the lung may depend on patient factors, such as the coordination between actuation of the device and inhalation through the delivery system.

AIRSUPRA also contains porous particles that form a co-suspension with the drug crystals. The porous particles are comprised of the phospholipid 1,2-distearoyl-sn-glycero-3-phosphocholine (DSPC) and calcium chloride. Porous particles and HFA-134a are excipients in the formulation.

12 CLINICAL PHARMACOLOGY

12.1 Mechanism of Action

AIRSUPRA contains both albuterol and budesonide; therefore, the mechanisms of action described below for the individual components apply to AIRSUPRA. These drugs represent two classes of medications (a short-acting selective beta2-adrenergic agonist and a synthetic corticosteroid) that have different effects on clinical, physiological, and inflammatory indices of asthma.

Albuterol

In vitro studies and in vivo pharmacologic studies have demonstrated that albuterol has a preferential effect on beta2-adrenergic receptors compared with isoproterenol. Although beta2-adrenoceptors are the predominant adrenergic receptors in bronchial smooth muscle and beta1-adrenoceptors are the predominant receptors in the heart, there are also beta2-adrenoceptors in the human heart comprising 10% to 50% of the total beta-adrenoceptors. The precise function of these receptors has not been established, but their presence raises the possibility that even selective beta2-agonists may have cardiac effects.

Activation of beta2-adrenergic receptors on airway smooth muscle leads to the activation of adenyl cyclase and to an increase in the intracellular concentration of cyclic-3′,5′-adenosine monophosphate (cyclic AMP). This increase of cyclic AMP leads to the activation of protein kinase A, which inhibits the phosphorylation of myosin and lowers intracellular ionic calcium concentrations, resulting in relaxation. Albuterol relaxes the smooth muscles of all airways, from the trachea to the terminal bronchioles. Albuterol acts as a functional antagonist to relax the airway irrespective of the spasmogen involved, thus protecting against all bronchoconstrictor challenges. Increased cyclic AMP concentrations are also associated with the inhibition of release of mediators from mast cells in the airway.

Albuterol has been shown in most controlled clinical trials to have more effect on the respiratory tract, in the form of bronchial smooth muscle relaxation, than isoproterenol at comparable doses while producing fewer cardiovascular effects. Controlled clinical studies and other clinical experience have shown that inhaled albuterol, like other beta-adrenergic agonist drugs, can produce a significant cardiovascular effect in some patients, as measured by pulse rate, blood pressure, symptoms, and/or electrocardiographic changes [see Warnings and Precautions (5.3)].

Budesonide

Budesonide is an anti-inflammatory corticosteroid that exhibits potent glucocorticoid activity and weak mineralocorticoid activity. In standard in vitro and animal models, budesonide has approximately a 200-fold higher affinity for the glucocorticoid receptor and a 1000-fold higher topical anti-inflammatory potency than cortisol (rat croton oil ear edema assay). As a measure of systemic activity, budesonide is 40 times more potent than cortisol when administered subcutaneously and 25 times more potent when administered orally in the rat thymus involution assay. The clinical significance of this is unknown.

In glucocorticoid receptor affinity studies, the 22R form was two times as active as the 22S epimer. In vitro studies indicated that the two forms of budesonide do not interconvert.

The precise mechanism of corticosteroid actions on inflammation in asthma is not known. Inflammation is an important component in the pathogenesis of asthma. Corticosteroids have a wide range of inhibitory activities against multiple cell types (e.g., mast cells, eosinophils, neutrophils, macrophages, and lymphocytes) and mediators (e.g., histamine, eicosanoids, leukotrienes, and cytokines) involved in allergic and non-allergic-mediated inflammation. These anti-inflammatory actions of corticosteroids may contribute to their efficacy in asthma.

Studies in asthmatic patients have shown a favorable ratio between topical anti-inflammatory activity and both genomic and non-genomic systemic corticosteroid effects over a wide range of doses of inhaled budesonide. This is explained by a combination of a relatively high local anti-inflammatory effect, extensive first pass hepatic degradation of orally absorbed drug (85-95%), and the low potency of formed metabolites (see below).

12.2 Pharmacodynamics

Albuterol

Albuterol has been shown in most controlled clinical trials to have more effect on the respiratory tract in the form of bronchial smooth muscle relaxation than isoproterenol at comparable doses while producing fewer cardiovascular effects. Controlled clinical studies and other clinical experience have shown that inhaled albuterol, like other beta-adrenergic agonist drugs, can produce a significant cardiovascular effect in some patients, as measured by pulse rate, blood pressure, symptoms, and/or electrocardiographic changes [see Warnings and Precautions (5.3)].

Budesonide

The therapeutic effects of conventional doses of orally inhaled budesonide are largely explained by its direct local action on the respiratory tract.

Inhaled budesonide has been shown to decrease airway reactivity in various challenge models, including histamine, methacholine, sodium metabisulfite, and adenosine monophosphate in patients with hyperreactive airways. The clinical relevance of these models is not certain.

HPA Axis Effects

AIRSUPRA, like other inhaled corticosteroid products, may impact the HPA axis, especially in susceptible individuals, in younger children, and in patients given high doses for prolonged periods [see Warnings and Precautions (5.10)].

The effects of AIRSUPRA on hypothalamic-pituitary-adrenal (HPA) axis were not studied in dedicated clinical trials.

The effects of inhaled AIRSUPRA 180 mcg/160 mcg and AS-BD MDI 180 mcg/80 mcg administered as 2 inhalations of 90 mcg/80 mcg or 90 mcg/40 mcg as needed in response to symptoms were studied on morning serum cortisol in 1254 patients with asthma between the ages of 4 and 84 years in MANDALA. Morning serum cortisol was collected at baseline, Week 24, end of study, or time of discontinuation. Morning cortisol concentration changes over time varied across treatment groups with mean changes from baseline to the Week 24 visit of ‑1.52 nmol/L, +5.43 nmol/L, and +15.42 nmol/L in the AIRSUPRA 180 mcg/160 mcg, AS-BD MDI 180 mcg/80 mcg, and AS MDI 180 mcg treatment groups, respectively.

12.3 Pharmacokinetics

The pharmacokinetics of AIRSUPRA and its individual components were evaluated in 3 studies in subjects 18 years of age and older (2 studies in healthy subjects and 1 study in patients with asthma). The pharmacokinetics of albuterol and budesonide from AIRSUPRA are comparable to the pharmacokinetics of albuterol and budesonide when administered as single dose of the individual components in studies of healthy subjects.

The pharmacokinetics presented below are primarily from studies conducted on AIRSUPRA and on its individual components, albuterol (AS MDI) and budesonide (BD MDI), also administered by the inhaled route.

Absorption

Albuterol
Healthy Subjects: Following inhaled administration of AIRSUPRA 180 mcg/160 mcg (administered as 2 inhalations of 90 mcg/80 mcg), the median tmax of albuterol was 1.00 hour (individual values ranged from 0.08 to 6.05 hours). Geometric mean Cmax was 472.2 pg/mL (individual values ranged from 38.4 to 971 pg/mL).

Asthma Patients: Following increasing cumulative doses (a total dose of 1440 mcg) of albuterol (AS MDI) and an active albuterol aerosol inhaler comparator in patients with asthma, mean albuterol plasma concentrations (at 15 minutes after dose) increased from predose levels (44.2 and 51.4 pg/mL) to 3278.0 pg/mL and 5241.7 pg/mL with AS MDI and the comparator, respectively. Results from this study indicate the total systemic exposure of albuterol was 21% (for AUC) and 27% (for Cmax) lower for AS MDI than for the comparator.

Budesonide
Healthy Subjects: Following inhaled administration in healthy subjects of AIRSUPRA 180 mcg/160 mcg (administered as 2 inhalations of 90 mcg/80 mcg), the median tmax of budesonide was 0.33 hours (individual values ranged from 0.08 to 4.00 hours). Geometric mean Cmax was 272.8 pg/mL (individual values ranged from 51.7 to 819 pg/mL). Systemic exposure to budesonide with AIRSUPRA did not exceed that from inhaled budesonide via a dry powder inhaler comparator in healthy subjects.

Distribution

Albuterol
Healthy Subjects: Following inhaled administration of AIRSUPRA 180 mcg/160 mcg (administered as 2 inhalations of 90 mcg/80 mcg), the mean apparent volume of distribution (Vz/F) of albuterol was 565.7 L.

Budesonide
Healthy Subjects: Following inhaled administration of AIRSUPRA 180 mcg/160 mcg (administered as 2 inhalations of 90 mcg/80 mcg), the mean apparent volume of distribution (Vz/F) of budesonide administered in AIRSUPRA was 1002 L.

Budesonide was 85-90% bound to plasma proteins. Protein binding was constant over the concentration range of 1‑100 nmol/L. Budesonide showed little or no binding to corticosteroid binding globulin. Budesonide rapidly equilibrated with red blood cells in a concentration independent manner with a blood/plasma ratio of about 0.8.

Elimination

Following inhaled single-dose administration with AIRSUPRA in healthy subjects, the mean terminal half-life of albuterol was estimated to be 7.1 hours (individual values ranged from 4.62 to 10.0 hours) and the mean terminal half-life of budesonide was estimated to be 4.1 hours (individual values ranges from 2.46 to 6.15 hours).

Metabolism

Albuterol
Information available in the published literature suggests that the primary enzyme responsible for the metabolism of albuterol in humans is SULTIA3 (sulfotransferase).

Budesonide
In vitro studies with human liver homogenates have shown that budesonide is rapidly and extensively metabolized. Two major metabolites formed via cytochrome P450 (CYP) isoenzyme 3A4 (CYP3A4) catalyzed biotransformation have been isolated and identified as 16α-hydroxyprednisolone and 6β-hydroxybudesonide. The corticosteroid activity of each of these two metabolites is less than 1% of that of the parent compound. No qualitative differences between the in vitro and in vivo metabolic patterns have been detected. Negligible metabolic inactivation was observed in human lung and serum preparations.

Excretion

Albuterol
The primary route of elimination of albuterol is through renal excretion of either the parent compound or the primary metabolite.

Budesonide
Budesonide is excreted in urine and feces in the form of metabolites. Approximately 60% of an intravenous radiolabeled dose was recovered in the urine. No unchanged budesonide was detected in the urine.

Specific Populations

Specific studies to examine the effects of age, sex, gender/ethnicity, or body weight on the pharmacokinetics of AIRSUPRA have not been conducted.

Patients with Renal or Hepatic Impairment
There are no data regarding the specific use of AIRSUPRA in patients with hepatic or renal impairment.

The effect of renal impairment on the pharmacokinetics of albuterol was evaluated in 5 patients with creatinine clearance of 7 to 53 mL/min, and the results were compared with those from healthy volunteers. Renal disease had no effect on the half-life, but there was a 67% decline in albuterol clearance. Caution should be used when administering high doses of AIRSUPRA to patients with renal impairment.

Reduced liver function may affect the elimination of corticosteroids. The pharmacokinetics of budesonide were affected by compromised liver function as evidenced by a doubled systemic availability after oral ingestion. The intravenous pharmacokinetics of budesonide were, however, similar in cirrhotic patients and in healthy subjects.

Drug Interaction Studies

Inhibitors of cytochrome P450 enzymes
Ketoconazole: As a strong inhibitor of cytochrome P450 (CYP) isoenzyme 3A4 (CYP3A4), the main metabolic enzyme for corticosteroids, ketoconazole increased plasma levels of orally ingested budesonide [see Warnings and Precautions (5.11), Drug Interactions (7.1)].

Cimetidine: At recommended doses, cimetidine, a nonspecific inhibitor of CYP enzymes, had a slight but clinically insignificant effect on the pharmacokinetics of oral budesonide.

13 NONCLINICAL TOXICOLOGY

13.1 Carcinogenesis, Mutagenesis, Impairment of Fertility

No studies of carcinogenicity, mutagenicity, or impairment of fertility were conducted with AIRSUPRA; however, available studies for the individual components, albuterol and budesonide, are described below. Findings are reported based on the MRHDID for albuterol and budesonide contained in AIRSUPRA.

Albuterol
In a 2-year study in Sprague-Dawley rats, albuterol sulfate caused a dose-related increase in the incidence of benign leiomyomas of the mesovarium at and above dietary doses of 2 mg/kg/day (approximately 15 times the MRHDID for adults on a mg/m^2 basis). In another study this effect was blocked by the coadministration of propranolol, a nonselective beta-adrenergic antagonist. In an 18-month study in CD-1 mice, albuterol sulfate showed no evidence of tumorigenicity at dietary doses of up to 500 mg/kg/day (approximately 1,900 times the MRHDID for adults on a mg/m^2 basis). In a 22-month study in Golden Hamsters, albuterol sulfate showed no evidence of tumorigenicity at dietary doses of up to 50 mg/kg/day (approximately 250 times the MRHDID for adults on a mg/m^2 basis).

Albuterol sulfate was not mutagenic in the Ames test or a mutation test in yeast. Albuterol sulfate was not clastogenic in a human peripheral lymphocyte assay or in an AH1 strain mouse micronucleus assay.

Reproduction studies in rats demonstrated no evidence of impaired fertility at oral doses up to 50 mg/kg/day (approximately 380 times the MRHDID for adults on a mg/m^2 basis).

Budesonide
In a 2-year study in Sprague-Dawley rats, budesonide caused a statistically significant increase in the incidence of gliomas in male rats receiving an oral dose of 50 mcg/kg/day (approximately 0.5 times the MRHDID in adults on a mcg/m^2 basis). No tumorigenicity was seen in male rats at oral doses up to 25 mcg/kg/day (approximately 0.5 times the MRHDID in adults on a mcg/m^2 basis) and in female rats at oral doses up to 50 mcg/kg/day (approximately 0.5 times the MRHDID doses in adults on a mcg/m^2 basis). In two additional 2-year studies in male Fischer and Sprague-Dawley rats, budesonide caused no gliomas at an oral dose of 50 mcg/kg/day (approximately 0.5 times the MRHDID in adults on a mcg/m^2 basis). However, in the male Sprague-Dawley rats, budesonide caused a statistically significant increase in the incidence of hepatocellular tumors at an oral dose of 50 mcg/kg/day (approximately 0.5 times the MRHDID in adults on a mcg/m^2 basis). The concurrent reference corticosteroids (prednisone and triamcinolone acetonide) in these two studies showed similar findings.

There was no evidence of a carcinogenic effect when budesonide was administered orally for 91 weeks to mice at doses up to 200 mcg/kg/day (equal to the MRHDID in adults on a mcg/m^2 basis). Budesonide was not mutagenic or clastogenic in six different test systems: Ames Salmonella/microsome plate test, mouse micronucleus test, mouse lymphoma test, chromosome aberration test in human lymphocytes, sex-linked recessive lethal test in Drosophila melanogaster, and DNA repair analysis in rat hepatocyte culture.

Fertility and reproductive performance were unaffected in rats at subcutaneous doses up to 80 mcg/kg/day (approximately 0.8 times the MRHDID in adults on a mcg/m^2 basis). At a subcutaneous dose of 20 mcg/kg/day (approximately 0.2 times the MRHDID in adults on a mcg/m^2 basis), decreases in maternal body weight gain, prenatal viability, and viability of the young at birth and during lactation were observed. No such effects were noted at 5 mcg/kg/day (approximately 0.05 times the MRHDID in adults on a mcg/m^2 basis).

14 CLINICAL STUDIES

The efficacy of AIRSUPRA was evaluated in MANDALA, DENALI and BATURA as described below. While patients 12 to 17 years of age were included in these trials, AIRSUPRA is not approved in this age group; therefore, efficacy results are presented for adults only.

MANDALA
The efficacy of AIRSUPRA 180 mcg/160 mcg was evaluated in patients 12 years of age and older with asthma in MANDALA (NCT03769090), a randomized, double-blind, multicenter study. MANDALA was a variable length exacerbation study with at least 24 weeks duration.

Patients 12 years of age and older were randomized (1:1:1) and received at least one dose of AIRSUPRA (AS-BD MDI 180 mcg/160 mcg), albuterol/budesonide (AS-BD MDI 180 mcg/80 mcg) or albuterol (AS MDI 180 mcg) as needed. Patients were required to be receiving medium to high dose ICS (inhaled corticosteroid) or low to high dose ICS/long-acting beta2-adrenergic agonists (LABA), with or without another controller medicine as maintenance therapy. All patients continued their own maintenance therapy throughout the trial. MANDALA was conducted in symptomatic patients with a history of at least 1 severe asthma exacerbation in the year prior to screening, pre-bronchodilator FEV1 40 to < 90% of predicted normal (for patients aged 12 to < 18 years old, ≥ 60%) and a confirmed reversibility to albuterol.

The adult efficacy population (n=2940) in MANDALA had a mean age of 52 years (range: 18-84 years), with 66% female and 82% White, and 25% of Hispanic or Latino ethnicity. The median duration of asthma was 21 years (range: 1 to 80 years) since the first diagnosis of asthma. The mean pre-bronchodilator percent predicted FEV1 was 63% (range: 33% - 101%).

The overall patterns of use of AIRSUPRA and AS MDI 180 mcg were similar during the randomized treatment period.

The primary efficacy endpoint was the time to first severe asthma exacerbation (defined as worsening or onset of asthma symptoms that required systemic corticosteroids for at least 3 days or an emergency room visit that led to the use of systemic corticosteroids for at least 3 days or a hospitalization for at least 24 hours due to asthma).

Efficacy results are shown for only the approved adult population. Treatment with AIRSUPRA, compared with AS MDI 180 mcg, demonstrated statistically significant reductions in the risk of severe asthma exacerbations among adult patients, as assessed by the time to first severe asthma exacerbation as described in Figure 1. Compared with AS MDI 180 mcg, patients receiving AIRSUPRA experienced a statistically significant 28% reduction (Hazard Ratio [HR]: 0.72; 95% CI: 0.60, 0.86) in the risk of a severe asthma exacerbation (p<0.001).

Figure 1. Kaplan-Meier Cumulative Incidence Curve for Time to First Exacerbation (MANDALA)^1

There were reductions in severe asthma exacerbation risk regardless of exacerbation history (1 or > 1 in the past year), baseline lung function, and asthma severity (defined by background maintenance therapy) compared with AS MDI 180 mcg.

Treatment with AIRSUPRA 180 mcg/160 mcg statistically significantly reduced the annual rate of severe asthma exacerbations by 24% compared with AS MDI 180 mcg as shown in Table 2.

Table 2 Annualized Rate of Severe Asthma Exacerbations (MANDALA)
 | Analysis Group | N | n | Number of Severe Exacerbations | Annualized Rate | Rate Ratio vs AS MDI (95% CI) | P-value
AIRSUPRA 180 mcg/160 mcg | ≥ 18 years | 979 | 198 (20%) | 324 | 0.46 | 0.76 (0.62, 0.93) | 0.008
AS MDI 180 mcg | ≥ 18 years | 980 | 259 (26%) | 403 | 0.60 | 0.76 (0.62, 0.93) | 0.008
N = number of adults in the efficacy population; n = number of adults who experienced at least one severe exacerbation

The annualized total systemic corticosteroid (SCS) dose due to asthma was calculated for each patient during the study period. For patients treated with AIRSUPRA 180 mcg/160 mcg the annualized total SCS dose when compared with AS MDI 180 mcg was statistically significantly different, with a reduction in mean annualized dose of 40 mg per patient [AIRSUPRA (87 mg) vs AS MDI 180 (127 mg)]. A total of 20% of adults on AIRSUPRA 180 mcg/160 mcg and 26% of adults on AS MDI 180 mcg received SCS due to asthma.

Asthma control was assessed using the Asthma Control Questionnaire (ACQ-5) responder analysis. Responders were defined as those patients with an improvement of 0.5 or more in overall ACQ-5 score at Week 24 compared to baseline. The percentage of ACQ-5 adult responders at Week 24 for AIRSUPRA 180 mcg/160 mcg was 67% compared with 63% for AS MDI 180 mcg (odds ratio: 1.21; 95% CI: 1.01, 1.46).

Asthma quality of life was assessed using the Asthma Quality of Life Questionnaire in patients 12 years of age and older (AQLQ+12). Responders were defined as those with an improvement of 0.5 or more in AQLQ score at Week 24 compared to baseline. The percentage of adult responders at Week 24 for AIRSUPRA 180 mcg/160 mcg was 52% compared with 47% for AS MDI 180 mcg (odds ratio: 1.22; 95% CI: 1.01, 1.47).

BATURA

The efficacy of AIRSUPRA was evaluated in 2421 patients 12 years of age and older with asthma who were previously treated with as-needed SABA alone, or as-needed SABA plus background maintenance of either low-dose ICS or LTRA, and self-reported use of a SABA for symptoms at least twice in the 2 weeks prior to enrollment.

BATURA (NCT05505734) was a randomized, double-blind, event-driven, multicenter study with a duration of 12 to 52 weeks. Patients were randomized (1:1) and received at least one dose of AIRSUPRA 180 mcg/160 mcg or AS MDI 180 mcg as needed. Patients enrolled on ICS or LTRA were instructed to continue their maintenance therapy throughout the study.

The adult efficacy population (n=2353) had a mean age of 44 years (range: 18 to 95 years) with 69% female, 70% White, 18% Black, and 12% of Hispanic or Latino ethnicity. In the year prior to screening, 11% of adults had at least one severe asthma exacerbation. Pre-study therapy for most adults (74%) was as-needed SABA alone.

The overall patterns of use of AIRSUPRA 180 mcg/160 mcg and AS MDI 180 mcg were similar during the randomized treatment period.

The primary efficacy endpoint was the time to first severe asthma exacerbation (defined as worsening or onset of asthma symptoms that required systemic corticosteroids for at least 3 days, an emergency room or urgent care visit that led to the use of systemic corticosteroids for at least 3 days, an in-patient hospitalization for at least 24 hours due to asthma, or death).

Efficacy results are presented for only the approved adult population. Compared with AS MDI 180 mcg, treatment with AIRSUPRA 180 mcg/160 mcg demonstrated a statistically significant 46% reduction in the risk of a first severe asthma exacerbation (Hazard Ratio [HR]: 0.54; 95% CI: 0.40, 0.72; p<0.001).

Treatment with AIRSUPRA 180 mcg/160 mcg also statistically significantly reduced the annualized rate of severe asthma exacerbations by 54% compared with AS MDI 180 mcg (rate ratio: 0.46; 95% CI: 0.33, 0.63; p<0.001) as shown in Table 3.

Table 3 Annualized Rate of Severe Asthma Exacerbations (BATURA)
 | Analysis Group | N | n | Number of Severe Exacerbations | Annualized Rate | Rate Ratio vs AS MDI (95% CI) | P-value
AIRSUPRA 180 mcg/160 mcg | ≥ 18 years | 1180 | 71 (6%) | 82 | 0.15 | 0.46 (0.33, 0.63) | <0.001
AS MDI 180 mcg | ≥ 18 years | 1173 | 126 (11%) | 159 | 0.33 | 0.46 (0.33, 0.63) | <0.001
N = number of adults in the efficacy population; n = number of adults who experienced at least one severe exacerbation

For adults treated with AIRSUPRA 180 mcg/160 mcg, the annualized total SCS dose when compared with AS MDI 180 mcg was statistically significantly different, with a reduction in the mean annualized dose of 40 mg per patient (AIRSUPRA [23 mg] vs AS MDI [63 mg]). A total of 6% of adults on AIRSUPRA 180 mcg/160 mcg and 11% of adults on AS MDI 180 mcg received SCS due to asthma.

DENALI

The efficacy of AIRSUPRA on lung function was evaluated in patients 12 years of age and older with asthma who were previously treated with as-needed SABA alone or with low-dose ICS maintenance therapy plus as-needed SABA. DENALI (NCT03847896) was a double-blind, active-comparator and placebo-controlled lung function study conducted over 12 weeks. Patients were randomized 1:1:1:1:1 to receive AIRSUPRA (AS-BD MDI 180 mcg/160 mcg), AS-BD MDI 180 mcg/80 mcg, BD MDI 160 mcg, AS MDI 180 mcg, or Placebo MDI, all administered 4 times daily. Only the results for the approved recommended dose of AIRSUPRA are described below.

The population 18 years of age and older (n=964) had a mean age of 50 years (range: 18-90 years) with 63% female and 89% White, and 28% of Hispanic or Latino ethnicity.

Efficacy results are presented for only the approved adult population. The onset of bronchodilation (as defined by a ≥ 15% increase in FEV1 post-dose within 30 minutes on Day 1) was observed in 51% of patients treated with AIRSUPRA 180 mcg/160 mcg and 43% of patients treated with AS MDI 180 mcg. Following a single dose on Day 1, the median time to onset and mean duration of bronchodilation were 7.5 and 186.9 minutes with AIRSUPRA 180 mcg/160 mcg and 10.0 and 167.9 minutes with AS MDI 180 mcg, respectively.

16 HOW SUPPLIED/STORAGE AND HANDLING

AIRSUPRA Inhalation Aerosol is supplied as a pressurized aluminum canister with an attached dose indicator and a white plastic actuator, with a frosted clear plastic dust cap tethered to it. Each canister is packaged in a foil overwrap pouch with a desiccant sachet and placed into a carton. Each carton contains one canister and a Patient Information leaflet. Each 120-inhalation canister has a net fill weight of 10.7 grams.

AIRSUPRA is available in the following package size as presented in Table 4:

Table 4 Package Information for AIRSUPRA
Package Size | Strength albuterol/budesonide | Number of Inhalations per Canister | NDC
AIRSUPRA | 90 mcg/80 mcg | 120 | 0310-9080-12

The AIRSUPRA canister should only be used with the AIRSUPRA actuator, and the AIRSUPRA actuator should not be used with any other inhalation drug product.

Counter

The correct amount of medication in each inhalation cannot be ensured after the labeled number of inhalations from the canister have been used, when the dose indicator pointer reaches zero, even though the canister may not feel completely empty. AIRSUPRA should be discarded when the dose indicator pointer reaches zero, or 12 months after removal of the foil pouch, whichever comes first. Never immerse the canister in water to determine the amount remaining in the canister (“float test”).

Storage

Store at controlled room temperature 20°C to 25°C (68°F to 77°F); excursions permitted to 15°C to 30°C (59°F to 86°F) [see USP]. Keep in a dry place away from heat and sunlight.

For best results, the canister should be at room temperature before use. Shake well before using. Keep out of reach of children.

Contents under pressure. Do not puncture. Do not use or store near heat or open flame. Exposure to temperatures above 49°C (120°F) may cause bursting. Never throw canister into fire or incinerator. Avoid spraying in eyes.

17 PATIENT COUNSELING INFORMATION

Advise the patient to read the FDA-approved patient labeling (Patient Information and Instructions for Use).

Deterioration of Asthma

Inform patients to seek medical attention immediately if treatment with AIRSUPRA becomes less effective for symptomatic relief, and/or symptoms become worse [see Warnings and Precautions (5.1)].

Paradoxical Bronchospasm

Instruct patients to discontinue AIRSUPRA and contact their healthcare provider right away if they develop paradoxical bronchospasm [see Warnings and Precautions (5.2)].

Do Not Exceed Recommended Dosage

Instruct patients concerning the recommended dosage of AIRSUPRA and not to exceed 6 doses (12 inhalations) in a 24-hour period [see Dosage and Administration (2.1), Warnings and Precautions (5.4)].

Hypersensitivity Reactions, Including Anaphylaxis

Advise patients to contact their healthcare provider and discontinue AIRSUPRA if hypersensitivity reactions (e.g., anaphylaxis, rash, urticaria, angioedema, and bronchospasm) occur with AIRSUPRA use [see Warnings and Precautions (5.5)].

Priming and Cleaning Inhaler

Instruct patients to prime the inhaler before using for the first time, when the inhaler has not been used for more than 7 days, is dropped, or after cleaning and to shake well before each spray.

To ensure proper dosing and to prevent actuator mouthpiece blockage, instruct patients how to clean the actuator [see Dosage and Administration (2.1) and Instructions for Use].

Use with Other Short-Acting Bronchodilators

Advise patients concerning the appropriate use of other short-acting bronchodilators while using AIRSUPRA [see Drug Interactions (7.2)].

Immunosuppression and Risk of Infections

Warn patients who are on immunosuppressant doses of corticosteroids to avoid exposure to chickenpox or measles and, if exposed, to consult their physician without delay. Patients should be informed of potential worsening of existing tuberculosis, fungal, bacterial, viral, or parasitic infections, or ocular herpes simplex [see Warnings and Precautions (5.8)].

Oropharyngeal Candidiasis

Patients should be advised that localized infections with Candida albicans occurred in the mouth and pharynx in some patients. Advise patients to rinse the mouth with water, if available, without swallowing after AIRSUPRA inhalation to help reduce the risk of thrush [see Warnings and Precautions (5.9)].

Hypercorticism and Adrenal Suppression

Advise patients that AIRSUPRA may cause systemic corticosteroid effects of hypercorticism and adrenal suppression [see Warnings and Precautions (5.10)].

Reduction in Bone Mineral Density

Advise patients who are at an increased risk for decreased BMD that the use of AIRSUPRA may pose an additional risk [see Warnings and Precautions (5.11)].

Glaucoma and Cataracts

Inform patients that long-term use of AIRSUPRA may increase the risk of increased intraocular pressure, glaucoma, and cataracts; consider regular eye examinations [see Warnings and Precautions (5.12)].

Pregnancy

Advise pregnant women that there is a pregnancy exposure registry that monitors pregnancy outcomes in women exposed to asthma medications during pregnancy and to contact the MotherToBaby Pregnancy Studies at 1-877-311-8972 or visit http://mothertobaby.org/pregnancy-studies/.

Manufactured for: AstraZeneca Pharmaceuticals LP, Wilmington, DE 19850
Manufactured by: AstraZeneca Dunkerque Production (AZDP),
Dunkerque, France

AIRSUPRA is a registered trademark of the AstraZeneca group of companies.
©AstraZeneca 2025

Patient Package Insert

PATIENT INFORMATION
AIRSUPRA® (ayr soo' prah)
(albuterol and budesonide)
inhalation aerosol, for oral inhalation use

What is AIRSUPRA?

AIRSUPRA combines 2 medicines, a short/rapid-acting beta2-adrenergic agonist (SABA) medicine (albuterol sulfate) and an inhaled corticosteroid (ICS) medicine (budesonide), in 1 inhaler, delivered as a propelled spray.

- SABA medicines such as albuterol help to relax the smooth muscles of the airways, causing the airways to widen, leading to easier breathing.
- ICS medicines such as budesonide help to decrease inflammation in the lungs. Inflammation in the lungs can lead to breathing difficulties.
- AIRSUPRA is a prescription medicine used:
  - as needed as a rescue inhaler to treat or prevent symptoms of asthma (tightening of the airways, wheezing, cough, and shortness of breath).
  - to help prevent sudden severe breathing problems (asthma attacks).
- AIRSUPRA is used as 2 inhalations (puffs) as needed. Do not use more than 12 inhalations (puffs) in a 24-hour period.
- AIRSUPRA is not to be used as maintenance treatment for asthma. If you are currently taking medicine long-term to maintain control of asthma symptoms, you should continue to take that medicine as directed by your healthcare provider.
- It is not known if AIRSUPRA is safe and effective in children.

Do not use AIRSUPRA if you:

- are allergic to albuterol sulfate, budesonide, or any of the other ingredients in AIRSUPRA. See the end of this Patient Information leaflet for a complete list of ingredients in AIRSUPRA.

Before using AIRSUPRA, tell your healthcare provider about all your medical conditions, including if you:

- have heart problems.
- have high blood pressure (hypertension).
- have convulsions (seizures).
- have thyroid problems.
- have diabetes.
- have low potassium levels in your blood.
- have an immune system problem.
- have or had tuberculosis of your respiratory tract.
- have had any type of viral, bacterial, parasitic, fungal infection, or herpes simplex infection of the eye (ocular herpes simplex) that has not been treated.
- have been exposed to chickenpox or measles or you have not received vaccines against these diseases.
- have or are at risk for weak bones. You are at risk for weak bones if you:
  - are inactive for a long period of time.
  - have a family history of osteoporosis.
  - are a woman going through menopause (“the change of life”) or are past menopause.
  - smoke or use tobacco.
  - are elderly.
  - do not eat well (poor nutrition).
  - use medicines that cause bone thinning (such as seizure medicines or corticosteroids) for a long time.
- have eye problems such as increased pressure in the eye, glaucoma, or cataracts.
- have liver problems.
- are pregnant or plan to become pregnant. It is not known if AIRSUPRA may harm your unborn baby.
  - Pregnancy Registry. There is a pregnancy registry for women who use asthma medicines during pregnancy. If you become pregnant, contact the MotherToBaby Pregnancy Studies conducted by the Organization of Teratology Information Specialists at 1-877-311-8972 or visit http://mothertobaby.org/pregnancy-studies/.
- are breastfeeding. It is not known if the medicines in AIRSUPRA pass into your breast milk and if they can harm your baby. You and your healthcare provider should decide if you will take AIRSUPRA while breastfeeding.

Tell your healthcare provider about all the medicines you take, including prescription and over-the-counter medicines, vitamins, and herbal supplements. AIRSUPRA and certain other medicines may affect each other causing side effects.

Especially, tell your healthcare provider if you take:

- medicines known as strong CYP3A4 inhibitors
- other inhaled medicines or asthma medicines
- beta blockers

- diuretics
- digoxin
- monoamine oxidase inhibitors
- tricyclic antidepressants

Ask your healthcare provider or pharmacist for a list of these medicines, if you are not sure.

Know the medicines that you take. Keep a list of them to show your healthcare provider and pharmacist each time you get a new medicine.

How should I use AIRSUPRA?
Read the step-by-step instructions for using AIRSUPRA at the end of this Patient Information leaflet.

- Before using AIRSUPRA, make sure your healthcare provider has taught you how to use the inhaler and that you understand how to use it correctly.
- Use AIRSUPRA exactly as your healthcare provider tells you to use it. Do not use AIRSUPRA more often than prescribed (no more than 12 puffs which equals 6 doses) within a 24-hour period.
- Do not change or stop other inhaled medicines or asthma medicines (oral or inhaled) without first talking to your healthcare provider.
- Call your healthcare provider or get emergency medical care right away if:
  - your breathing problems get worse.
  - you need to use AIRSUPRA more often than usual.
  - AIRSUPRA does not work as well to relieve your asthma.

What are the possible side effects of AIRSUPRA?
AIRSUPRA can cause serious side effects, including:

- worsening trouble breathing, coughing, and wheezing (paradoxical bronchospasm). If this happens, stop using AIRSUPRA and call your healthcare provider or get emergency medical care right away. Paradoxical bronchospasm is more likely to happen with your first use of a new canister of medicine.
- heart problems, including faster heart rate and higher blood pressure.
- possible death in people who use too much AIRSUPRA.
- serious allergic reactions. Tell your healthcare provider or get emergency medical care right away if you have:
  - skin rash, redness, or swelling
  - severe itching
  - swelling of the face, mouth, and tongue
  - trouble breathing or swallowing
  - chest pain
- changes in laboratory blood levels. Low levels of potassium (hypokalemia) may cause abnormal heart rhythms. Your healthcare provider may do blood tests to check your potassium levels during treatment with AIRSUPRA.
- weakened immune system and increased chance of getting infections. Tell your healthcare provider about any signs and symptoms of infection including:

- fever
- pain

- aches
- chills

- feeling tired
- nausea and vomiting

- fungal infection in your mouth and throat (thrush). This is a common side effect. Rinse your mouth with water, if available, without swallowing after using AIRSUPRA to help reduce your chance of getting thrush.
- reduced adrenal function (adrenal insufficiency). Adrenal insufficiency is a condition in which the adrenal glands do not make enough steroid hormones. This can happen when you start taking a medicine containing an ICS (such as AIRSUPRA). When your body is under stress from fever, trauma (such as a car accident), infection or surgery, adrenal insufficiency can get worse.
  Symptoms of adrenal insufficiency include:

- feeling tired
- lack of energy

- weakness
- nausea and vomiting

- low blood pressure

- bone thinning or weakness (osteoporosis). Your healthcare provider should check you for this during treatment with AIRSUPRA.
- eye problems, including glaucoma and cataracts. You should have regular eye exams while using AIRSUPRA.

Call your healthcare provider or get medical help right away if you have symptoms of any of the serious side effects listed above.
Common side effects of AIRSUPRA include:

  - headache
  - cough
  - hoarseness

Tell your healthcare provider about any side effect that bothers you or that does not go away.

These are not all the side effects of AIRSUPRA. For more information, ask your healthcare provider or pharmacist.

Call your doctor for medical advice about side effects. You may report side effects to FDA at 1-800-FDA-1088. You may also report side effects to AstraZeneca at 1-800-236-9933.

How should I store AIRSUPRA?

- Store AIRSUPRA at room temperature between 68ºF to 77ºF (20ºC to 25ºC). Keep in a dry place away from heat and sunlight.
- Store AIRSUPRA in the unopened foil pouch and only open when ready for use.
- Do not put a hole in the AIRSUPRA canister.
- Do not use or store AIRSUPRA near heat or a flame. Temperatures above 120ºF (49ºC) may cause the canister to burst.
- Do not throw the AIRSUPRA canister into a fire or an incinerator.
- Throw away AIRSUPRA 12 months after you open the foil pouch or when the puff indicator reaches zero “0”, whichever comes first.

Keep AIRSUPRA and all medicines out of the reach of children.

General information about the safe and effective use of AIRSUPRA
Medicines are sometimes prescribed for purposes other than those listed in a Patient Information leaflet. Do not use AIRSUPRA for a condition for which it was not prescribed. Do not give your AIRSUPRA to other people, even if they have the same condition that you have. It may harm them.
You can ask your pharmacist or healthcare provider for information about AIRSUPRA that is written for healthcare professionals.

What are the ingredients in AIRSUPRA?

Active ingredients: micronized albuterol sulfate and micronized budesonide.

Inactive ingredients: hydrofluoroalkane (HFA-134a) and porous particles 1,2-Distearoyl-sn-glycero-3-phosphocholine (DSPC) and calcium chloride.
AIRSUPRA is a registered trademark of the AstraZeneca group of companies ©AstraZeneca 2025

Manufactured for: AstraZeneca Pharmaceuticals LP, Wilmington, DE 19850; Manufactured by: AstraZeneca Dunkerque Production (AZDP), Dunkerque, France

For more information, go to www.AIRSUPRA.com or call 1-800-236-9933.

This Patient Information has been approved by the U.S. Food and Drug Administration Revised: September 2025

Instructions for Use

AIRSUPRA® (ayr soo' prah)
(albuterol and budesonide)
inhalation aerosol, for oral inhalation use
120-inhalation canister

Read this Instructions for Use before you start using AIRSUPRA and each time you get a new refill. There may be new information. This information does not take the place of talking to your healthcare provider about your medical condition or treatment.

Important information

- For oral inhalation use only.
- Use AIRSUPRA exactly as your healthcare provider tells you to.
- Before you use AIRSUPRA for the first time, you will need to prime it.
- Rinse the white actuator 1-time each week so that the medicine does not build up and block the spray through the mouthpiece.
- 2 puffs of medicine is 1-dose. Do not use more than 6 doses (12 puffs) in a 24-hour period.
- Rinse your mouth with water, if available, after using AIRSUPRA to decrease the chance of getting a fungal infection (thrush) in your mouth and throat.

Parts of your AIRSUPRA inhaler

Reading the puff indicator

- The puff indicator will count down by 1 each time you spray a puff of medicine.

Do not try to take a puff of medicine when the pointer is at 0 because you will not receive a full dose.

Before using your AIRSUPRA inhaler

1. Write the Use by date

Write the Use By Date (the date 12 months after you open the foil pouch) on the actuator label using permanent ink. For example, if you open the foil pouch on March 1, you will write March 1 on the actuator label.

Write the Use By Date on the actuator label.

2. Prime your AIRSUPRA inhaler before first use
Take the cover off the mouthpiece by squeezing both sides of the cover while pulling it down. | Shake the inhaler well. Hold your AIRSUPRA inhaler facing away from you and press down firmly on the top of the puff indicator to spray 1 test-puff into the air. Repeat the priming steps for a total of 4 test-puffs. Shake your AIRSUPRA inhaler before each test-puff.
Extra puffs are provided for priming. Do not skip priming.

When and how to re-prime your AIRSUPRA inhaler
Re-prime your inhaler:; - if it is not used for more than 7 days. - if it is dropped - after rinsing white actuator | To re-prime your inhaler:; Take the cover off the mouthpiece and spray 2 test-puffs into the air. Shake your AIRSUPRA inhaler before each test-puff.
Extra puffs are provided for priming. Do not skip priming.

Inhaling your medicine

1. Check

Take the cover off the mouthpiece. Check the mouthpiece for foreign objects and remove objects before use.

Check inside mouthpiece.

2. Shake and Inhale

Shake well

Breathe out fully

Place the mouthpiece into your mouth and close your lips around the mouthpiece.

Start to breathe in
deeply and slowly
while spraying 1 puff.
Continue breathing in
until you cannot anymore.

Remove the mouthpiece from your mouth. Hold your breath for as long as you can or up to 10 seconds.

3. Repeat | 4. Place the mouthpiece cover back on | 5. Rinse
Immediately repeat the shake and inhale step to take a second puff. | Place the mouthpiece cover back on the mouthpiece. | Rinse your mouth with water, if available (Do not swallow the water).
2 puffs equals 1 dose.

Rinsing your actuator 1 time each week

1. Remove canister

Remove the canister and set it aside. Take the cover off the mouthpiece. Do not allow the canister to get wet.

2. Rinse through both ends

Rinse each end of the actuator with warm water for 30 seconds. Shake off as much water as you can. Do not use soap. Do not dry with a towel or tissue.

Look into the mouthpiece and actuator to make sure any medicine build-up has been completely washed away. If there is any build-up, repeat the weekly rinse step 2 again.

Check inside
mouthpiece
and actuator.

3. Air-dry

Let the actuator air-dry, such as overnight.

4. Re-assemble and re-prime

Re-assemble AIRSUPRA when the actuator is fully dry.

First, place the mouthpiece cover back on. After the mouthpiece cover is on, gently press the canister down into actuator. Do not insert the canister while the mouthpiece cover is off.

Re-prime the inhaler by following the Re-prime steps above.

Emergency inhaler use when wet

If you need to use the inhaler before it is dry:

- shake off as much excess water as you can
- insert the canister into the actuator
- shake and spray 2-test puffs into the air away from your face
- take the prescribed dose
- rinse the actuator again following the Weekly Rinse steps

Storing your inhaler

- Store your inhaler at room temperature between 68°F to 77°F (20°C to 25°C).
- Do not store in a humid environment, such as a bathroom.
- Keep your inhaler and all medicines out of the reach of children.

Throwing away your AIRSUPRA inhaler

Throw away your AIRSUPRA inhaler in the household trash:

- when the puff indicator reaches zero “0” or 12 months after you open the foil pouch, whichever comes first.

Do not reuse or use the actuator with medicine canisters from other inhalers.
Do not puncture or throw the canister into a fire or incinerator.

Ordering a new AIRSUPRA inhaler

- Order a new AIRSUPRA inhaler when the pointer on the puff indicator is in the yellow zone.

This Instructions for Use has been approved by the U.S. Food and Drug Administration

Revised: September 2025

Instructions for Use

AIRSUPRA® (ayr soo' prah)
(albuterol and budesonide)
inhalation aerosol, for oral inhalation use
28-inhalation canister

Read this Instructions for Use before you start using AIRSUPRA and each time you get a new refill. There may be new information. This information does not take the place of talking to your healthcare provider about your medical condition or treatment.

Important information

- For oral inhalation use only.
- Use AIRSUPRA exactly as your healthcare provider tells you to.
- Before you use AIRSUPRA for the first time, you will need to prime it.
- Rinse the white actuator 1-time each week so that the medicine does not build up and block the spray through the mouthpiece.
- 2 puffs of medicine is 1-dose. Do not use more than 6 doses (12 puffs) in a 24-hour period.
- Rinse your mouth with water, if available, after using AIRSUPRA to decrease the chance of getting a fungal infection (thrush) in your mouth and throat.

Parts of your AIRSUPRA inhaler

Reading the puff indicator

- The puff indicator will count down by 1 each time you spray a puff of medicine.

Do not try to take a puff of medicine when the pointer is at 0 because you will not receive a full dose.

Before using your AIRSUPRA inhaler

1. Write the Use by date

Write the Use By Date (the date 6 months after you open the foil pouch) on the actuator label using permanent ink. For example, if you open the foil pouch on March 1, you will write September 1 on the actuator label.

Write the Use By Date on the actuator label.

2. Prime your AIRSUPRA inhaler before first use
Take the cover off the mouthpiece by squeezing both sides of the cover while pulling it down. | Shake the inhaler well. Hold your AIRSUPRA inhaler facing away from you and press down firmly on the top of the puff indicator to spray 1 test-puff into the air. Repeat the priming steps for a total of 4 test-puffs. Shake your AIRSUPRA inhaler before each test-puff.
Extra puffs are provided for priming. Do not skip priming.

When and how to re-prime your AIRSUPRA inhaler
Re-prime your inhaler:; - if it is not used for more than 7 days. - if it is dropped - after rinsing white actuator | To re-prime your inhaler:; Take the cover off the mouthpiece and spray 2 test-puffs into the air. Shake your AIRSUPRA inhaler before each test-puff.
Extra puffs are provided for priming. Do not skip priming.

Inhaling your medicine

1. Check

Take the cover off the mouthpiece. Check the mouthpiece for foreign objects and remove objects before use.

Check inside mouthpiece.

2. Shake and Inhale

Shake well

Breathe out fully

Place the mouthpiece into your mouth and close your lips around the mouthpiece.

Start to breathe in
deeply and slowly
while spraying 1 puff.
Continue breathing in
until you cannot anymore.

Remove the mouthpiece from your mouth. Hold your breath for as long as you can or up to 10 seconds.

3. Repeat | 4. Place the mouthpiece cover back on | 5. Rinse
Immediately repeat the shake and inhale step to take a second puff. | Place the mouthpiece cover back on the mouthpiece. | Rinse your mouth with water, if available (Do not swallow the water).
2 puffs equals 1 dose.

Rinsing your actuator 1 time each week

1. Remove canister

- Remove the canister and set it aside. Take the cover off the mouthpiece. Do not allow the canister to get wet.

2. Rinse through both ends

Rinse each end of the actuator with warm water for 30 seconds. Shake off as much water as you can. Do not use soap. Do not dry with a towel or tissue.

Look into the mouthpiece and actuator to make sure any medicine build-up has been completely washed away. If there is any build-up, repeat the weekly rinse step 2 again.

Check inside
mouthpiece
and actuator.

3. Air-dry

Let the actuator air-dry, such as overnight.

4. Re-assemble and re-prime

Re-assemble AIRSUPRA when the actuator is fully dry.

First, place the mouthpiece cover back on. After the mouthpiece cover is on, gently press the canister down into actuator. Do not insert the canister while the mouthpiece cover is off.

Re-prime the inhaler by following the Re-prime steps above.

Emergency inhaler use when wet

If you need to use the inhaler before it is dry:

- shake off as much excess water as you can
- insert the canister into the actuator
- shake and spray 2-test puffs into the air away from your face
- take the prescribed dose
- rinse the actuator again following the Weekly Rinse steps

Storing your inhaler

- Store your inhaler at room temperature between 68°F to 77°F (20°C to 25°C).
- Do not store in a humid environment, such as a bathroom.
- Keep your inhaler and all medicines out of the reach of children.

Throwing away your AIRSUPRA inhaler

Throw away your AIRSUPRA inhaler in the household trash:

- when the puff indicator reaches zero “0” or 6 months after you open the foil pouch, whichever comes first.

Do not reuse or use the actuator with medicine canisters from other inhalers.
Do not puncture or throw the canister into a fire or incinerator.

Ordering a new AIRSUPRA inhaler

- Order a new AIRSUPRA inhaler when the pointer on the puff indicator is in the yellow zone.

This Instructions for Use has been approved by the U.S. Food and Drug Administration

Revised: September 2025

Package/Label Display Panel

NDC 0310-9080-12 Rx only

AIRSUPRA®

(albuterol and budesonide)

inhalation aerosol

90 mcg/80 mcg

Per inhalation

For Oral Inhalation only

Shake inhaler well before using

120 inhalations

AstraZeneca

AIRSUPRA®

(albuterol and budesonide)

inhalation aerosol

90 mcg/80 mcg

Per inhalation